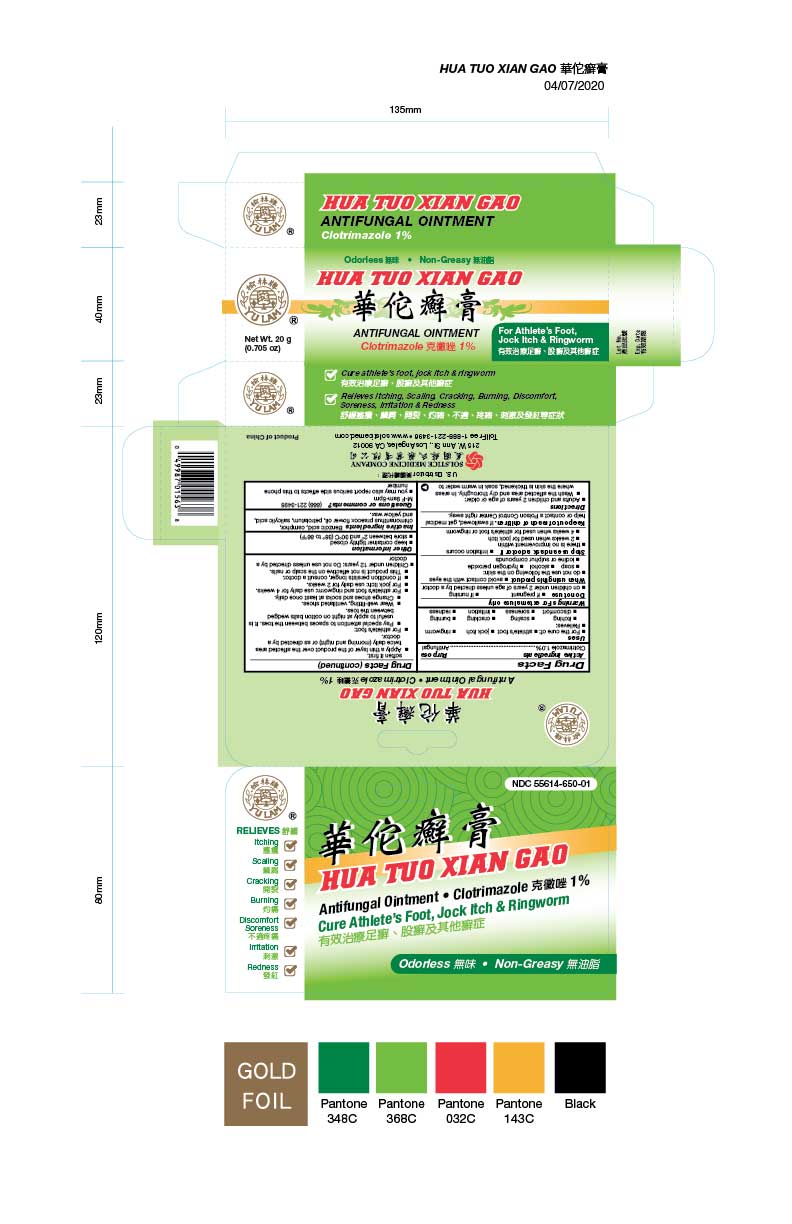 DRUG LABEL: HUA TUO XIAN GAO ANTIFUNGAL
NDC: 55614-650 | Form: OINTMENT
Manufacturer: MADISON ONE ACME INC
Category: otc | Type: HUMAN OTC DRUG LABEL
Date: 20251110

ACTIVE INGREDIENTS: CLOTRIMAZOLE 1 g/100 g
INACTIVE INGREDIENTS: BENZOIC ACID; CAMPHOR (SYNTHETIC); CHIMONANTHUS PRAECOX FLOWER OIL; PETROLATUM; SALICYLIC ACID; YELLOW WAX

Drug Facts

Active ingredient
Clotrimazole 1.0%

Purpose
Antifungal

Uses
■ For the cure of:
■ athlete’s foot
■ jock itch
■ ringworm
■ Relieves:
■ itching
■ scaling
■ cracking
■ burning
■ discomfort
■ soreness
■ irritation
■ redness

Warnings
For external use only

Do not use
■ if pregnant
■ if nursing
■ on children under 12 years of age unless directed by a doctor

When using this product
■ avoid contact with the eyes
■ do not use the following on the skin:
■ soap
■ alcohol
■ hydrogen peroxide
■ iodine or sulphur compounds

Stop use and ask a doctor if
■ irritation occurs
■ there is no improvement within
■ 2 weeks when used for jock itch
■ 4 weeks when used for athlete’s foot or ringworm

Keep out of reach of children.
If swallowed, get medical help or contact a Poison Control Center right away.

Directions
■ Adults and children 12 years of age or older:
■ Wash the affected area and dry thoroughly. In areas where the skin is thickened, soak in warm water to soften it first
■ Apply a thin layer of the product over the affected area twice daily (morning and night) or as directed by a doctor.
■ For athlete’s foot:
■ Pay special attention to spaces between the toes. It is useful to apply at night on cotton balls wedged between the toes.
■ Wear well-fitting, ventilated shoes.
■ Change shoes and socks at least once daily.
■ For athlete’s foot and ringworm: use daily for 4 weeks.
■ For jock itch: use daily for 2 weeks.
■ If condition persists longer, consult a doctor.
■ This product is not effective on the scalp or nails.
■ Children under 12 years: Do not use unless directed by a doctor

Other information
■ keep container tightly closed
■ store between 2º and 30º C (36º to 86º F)

Inactive ingredients
Benzoic acid, camphor, chimonanthus praecox flower oil, petrolatum, salicylic acid, and yellow wax.

Questions or comments?
(888) 221-3496 M-F 9am-5pm
■ you may also report serious side effects to this phone number

PACKAGE LABEL

HUA TUO XIAN GAO ANTIFUNGAL OINTMENT

Clotrimazole 1.0%

Cure Athlete’s Foot Jock Itch & Ringworm

NDC 55614-650-01

20 g (0.7 oz)

Odorless

Non-Greasy